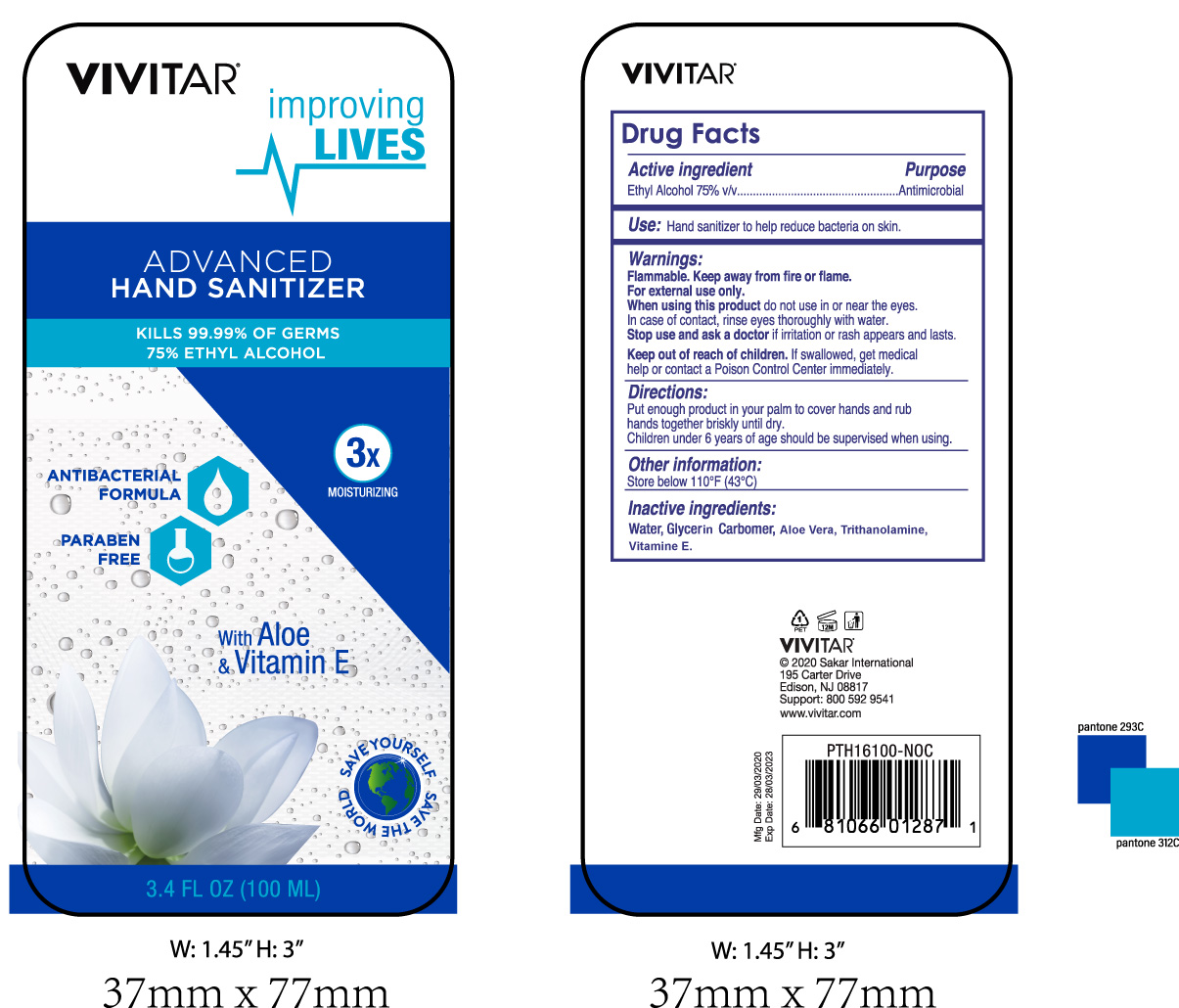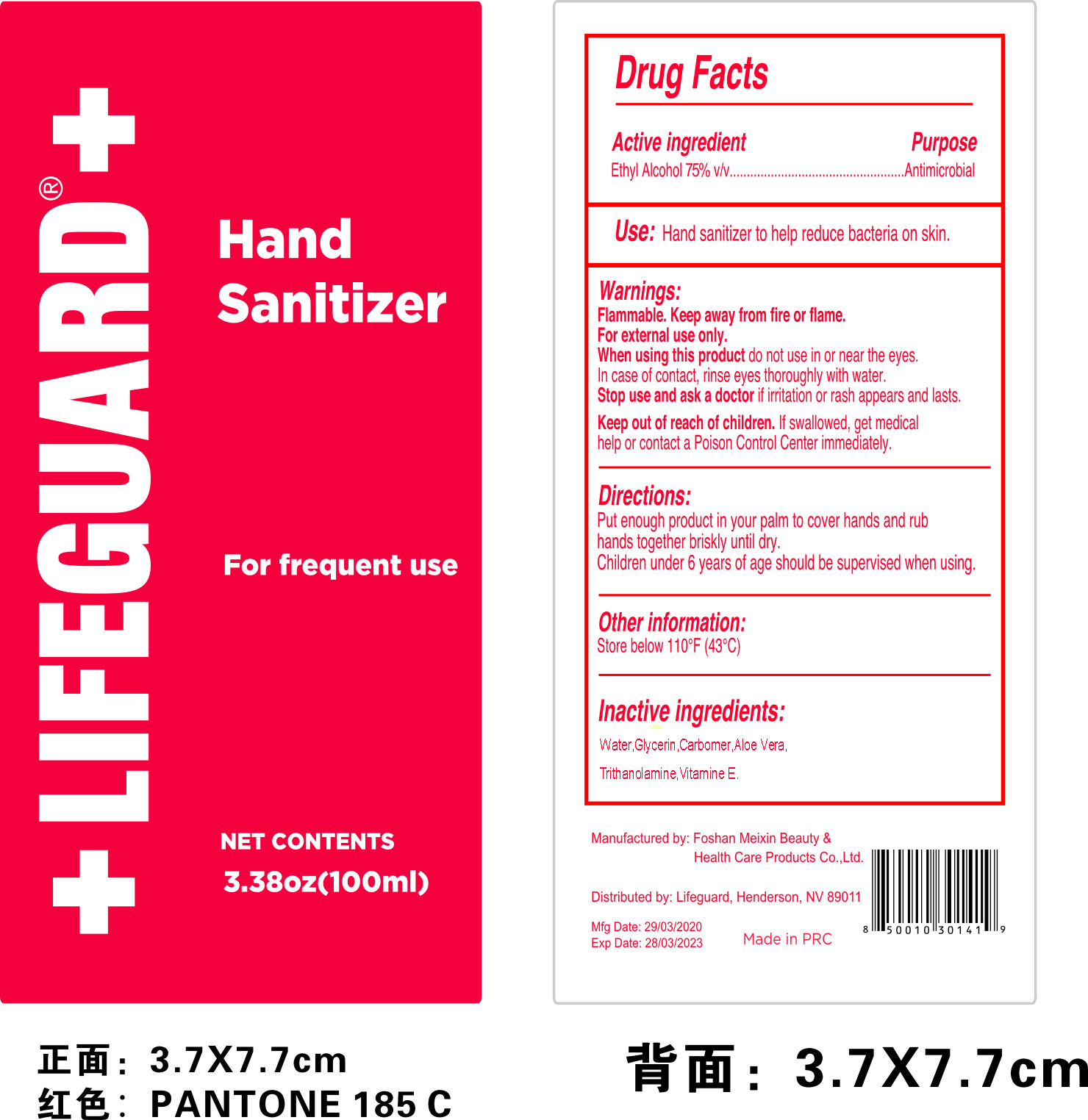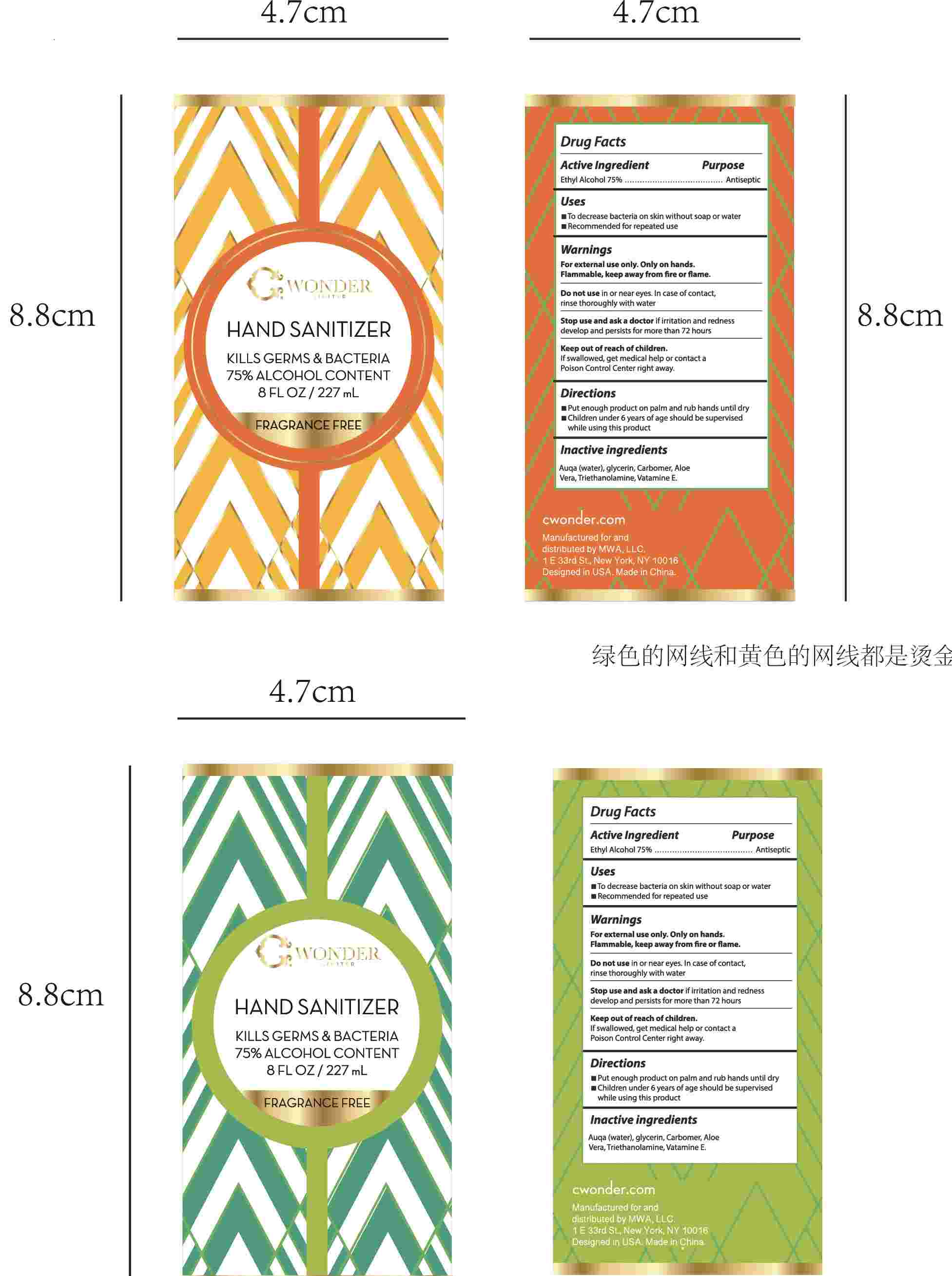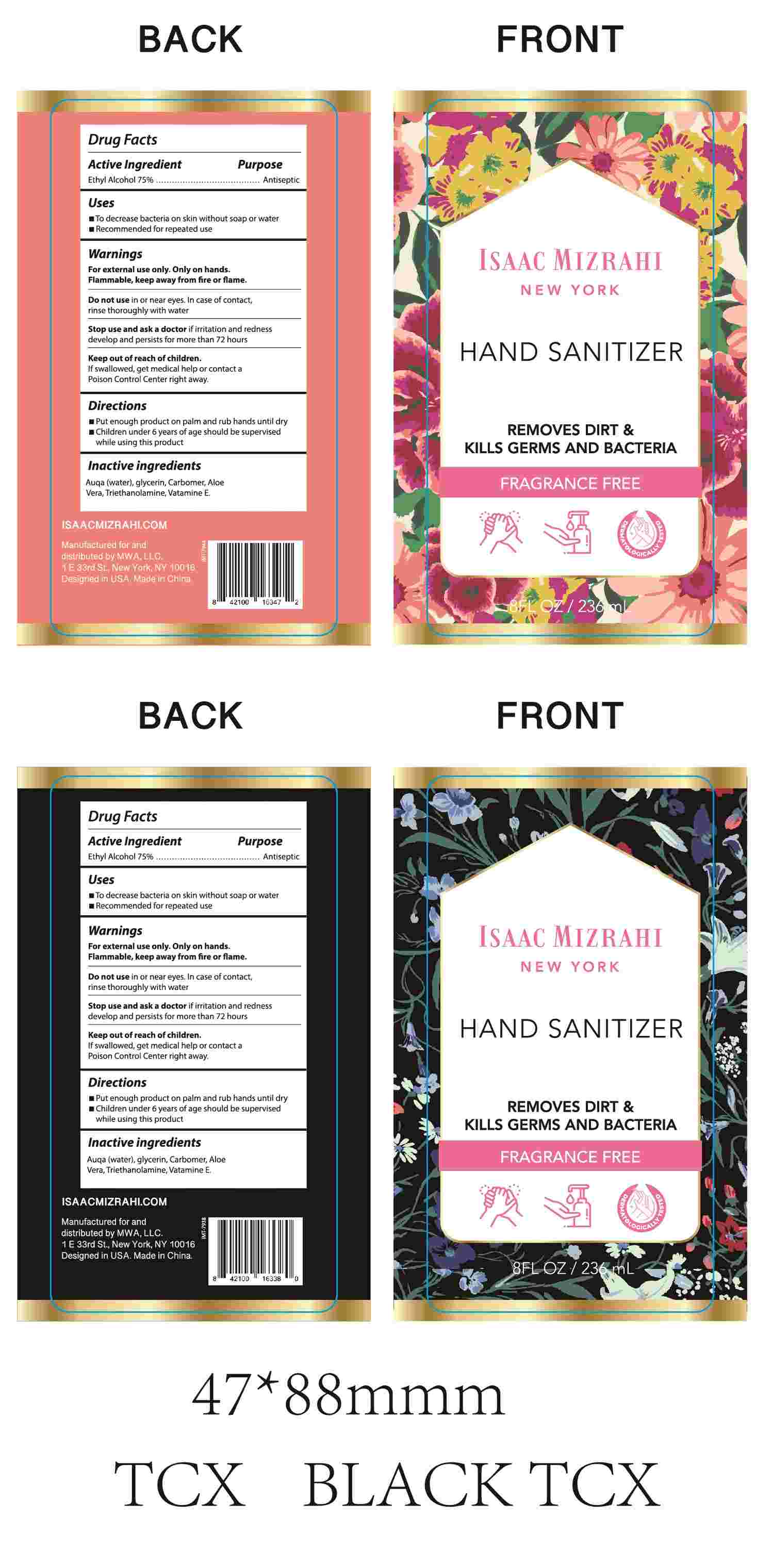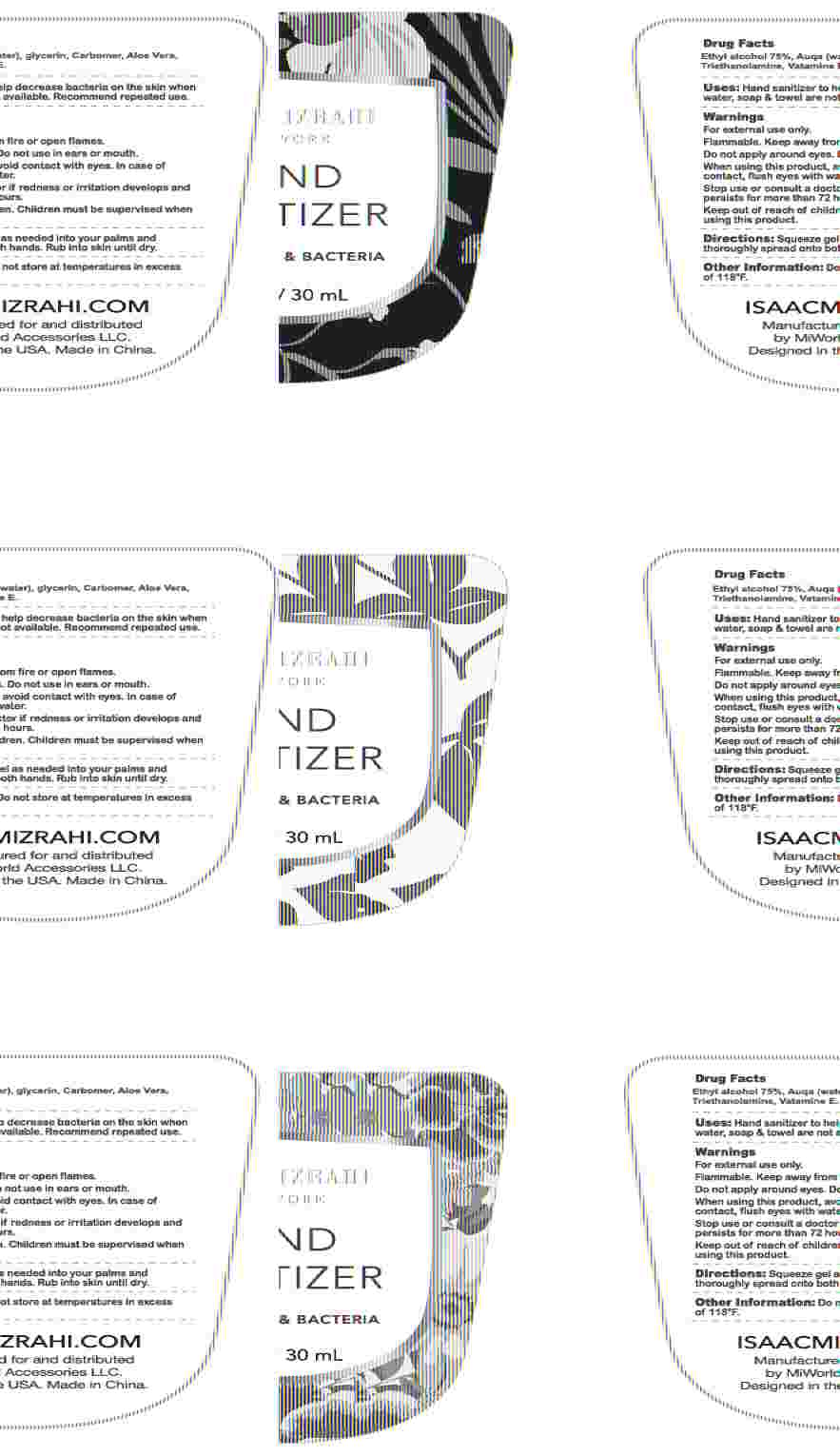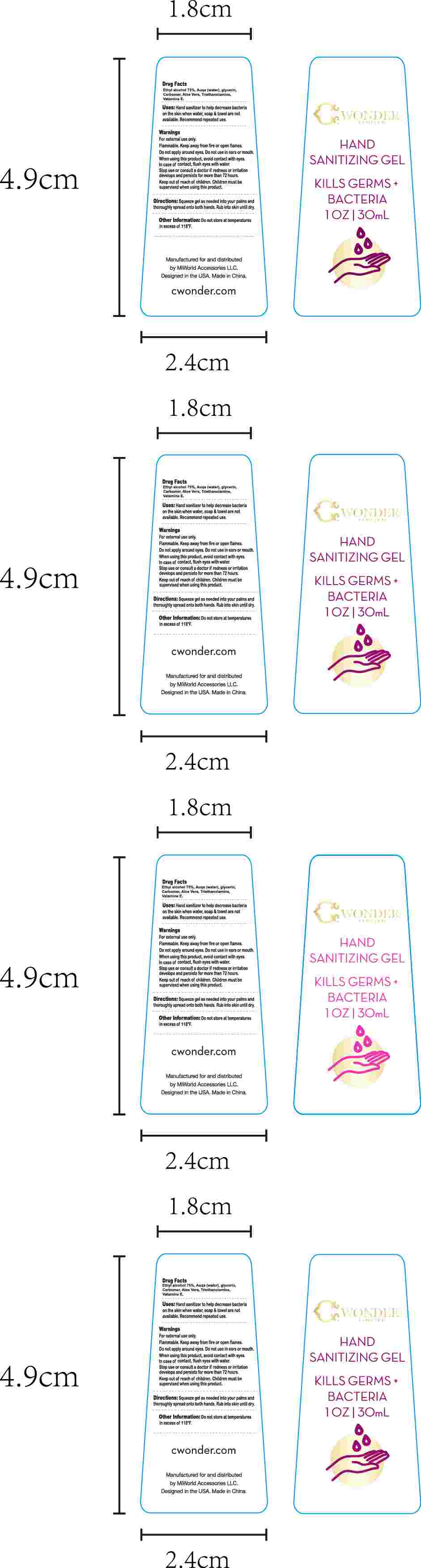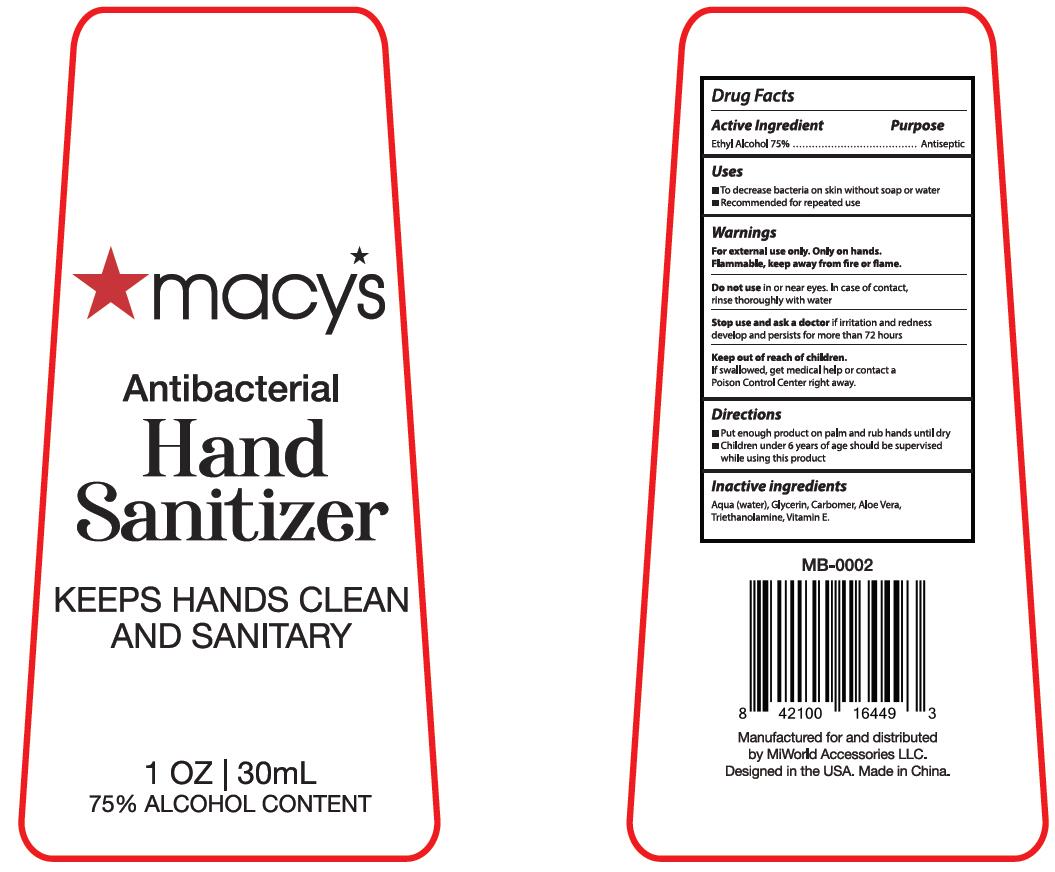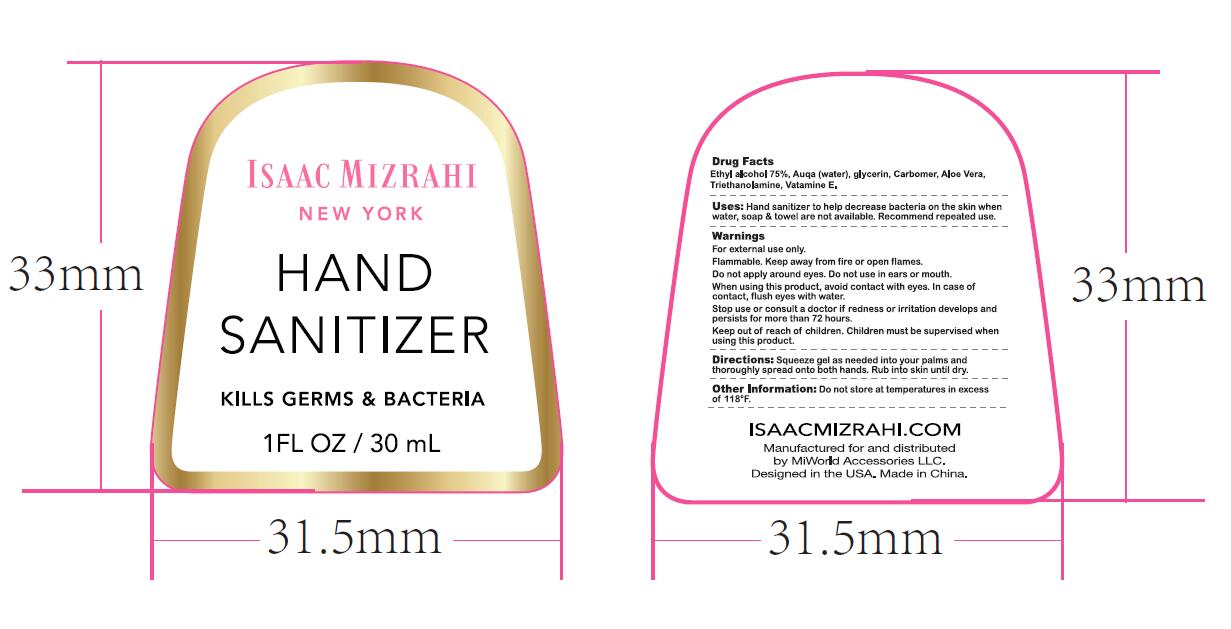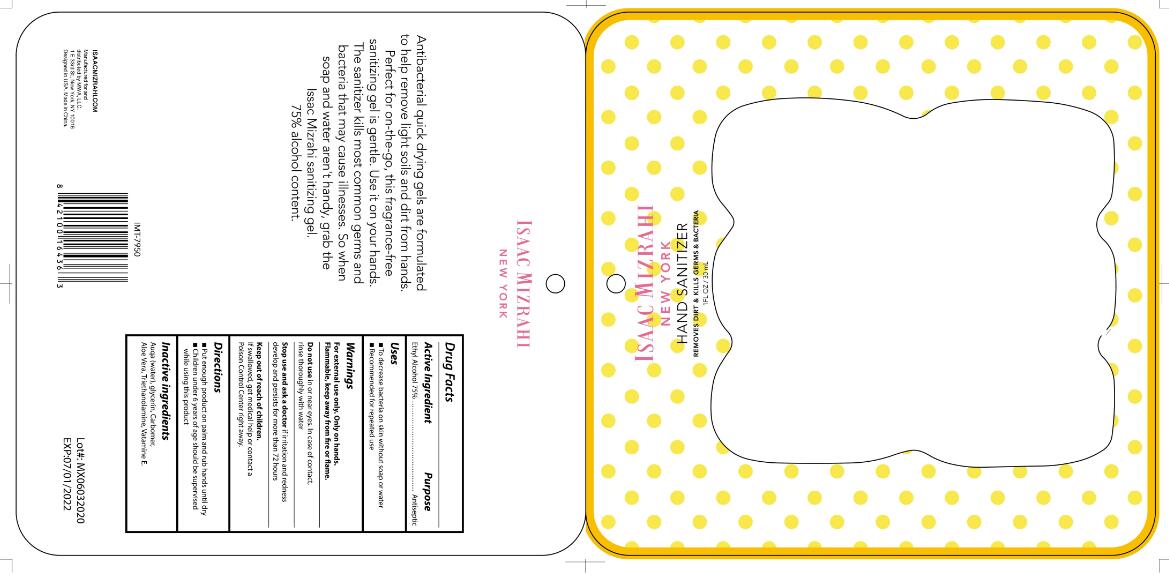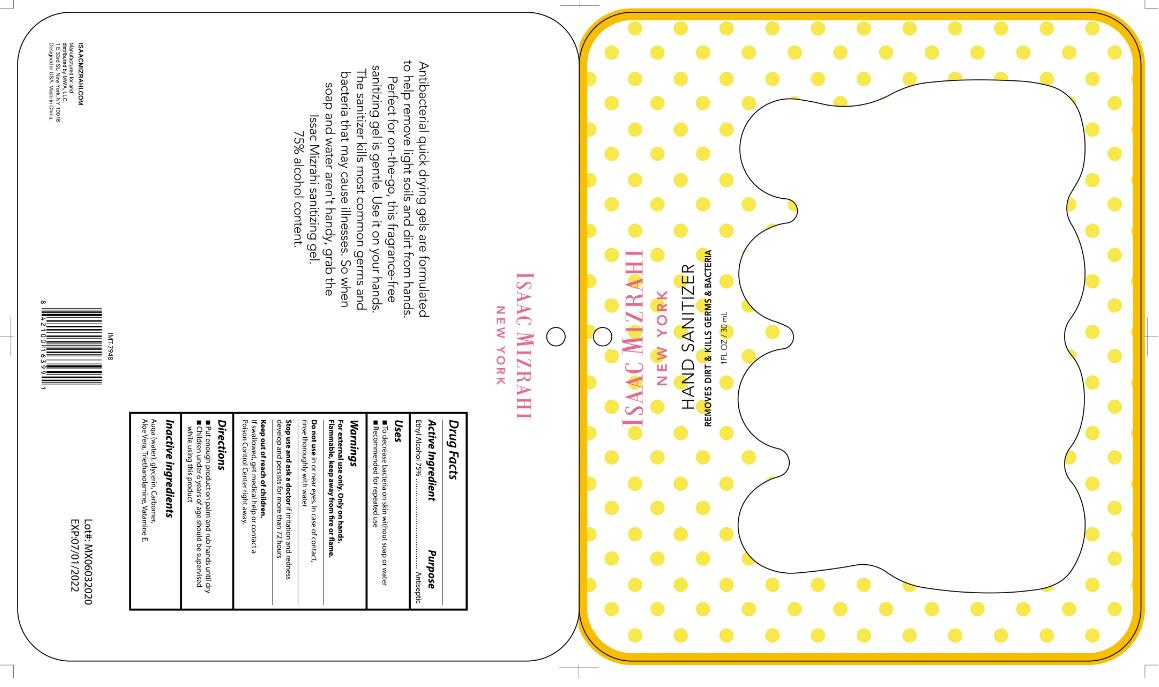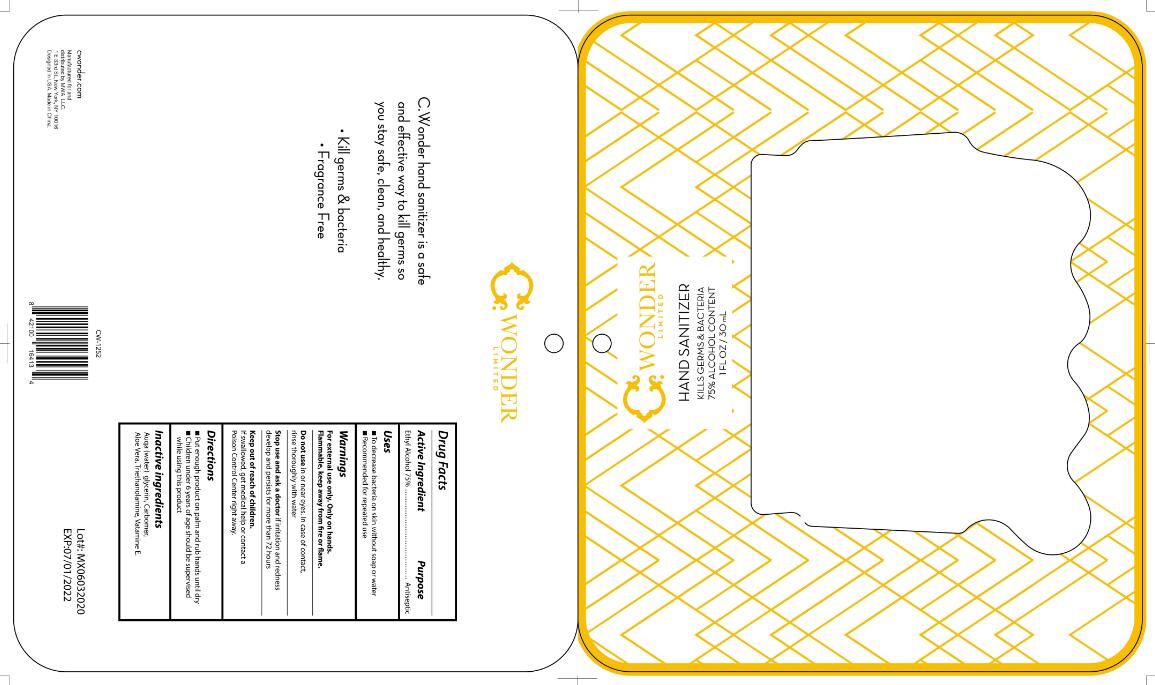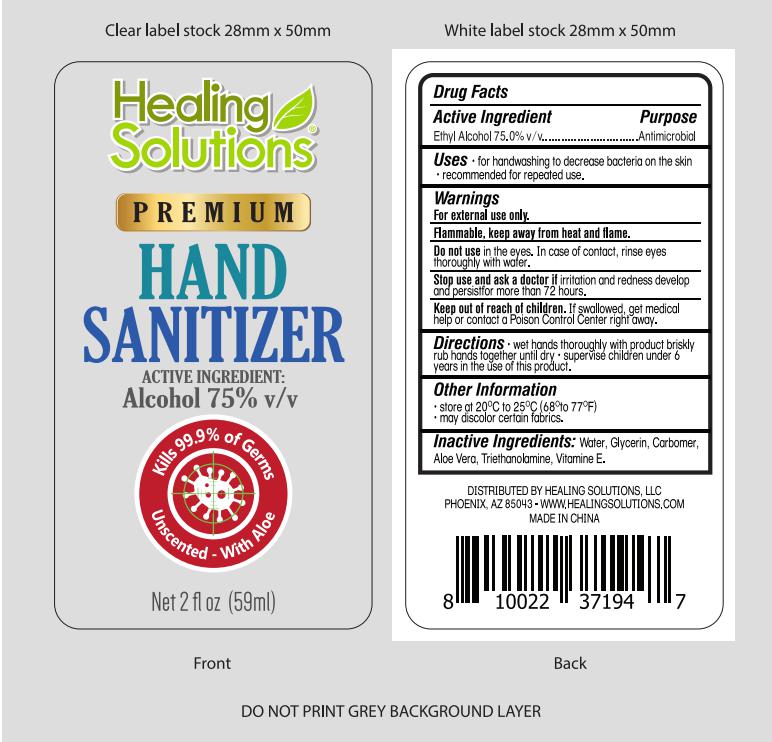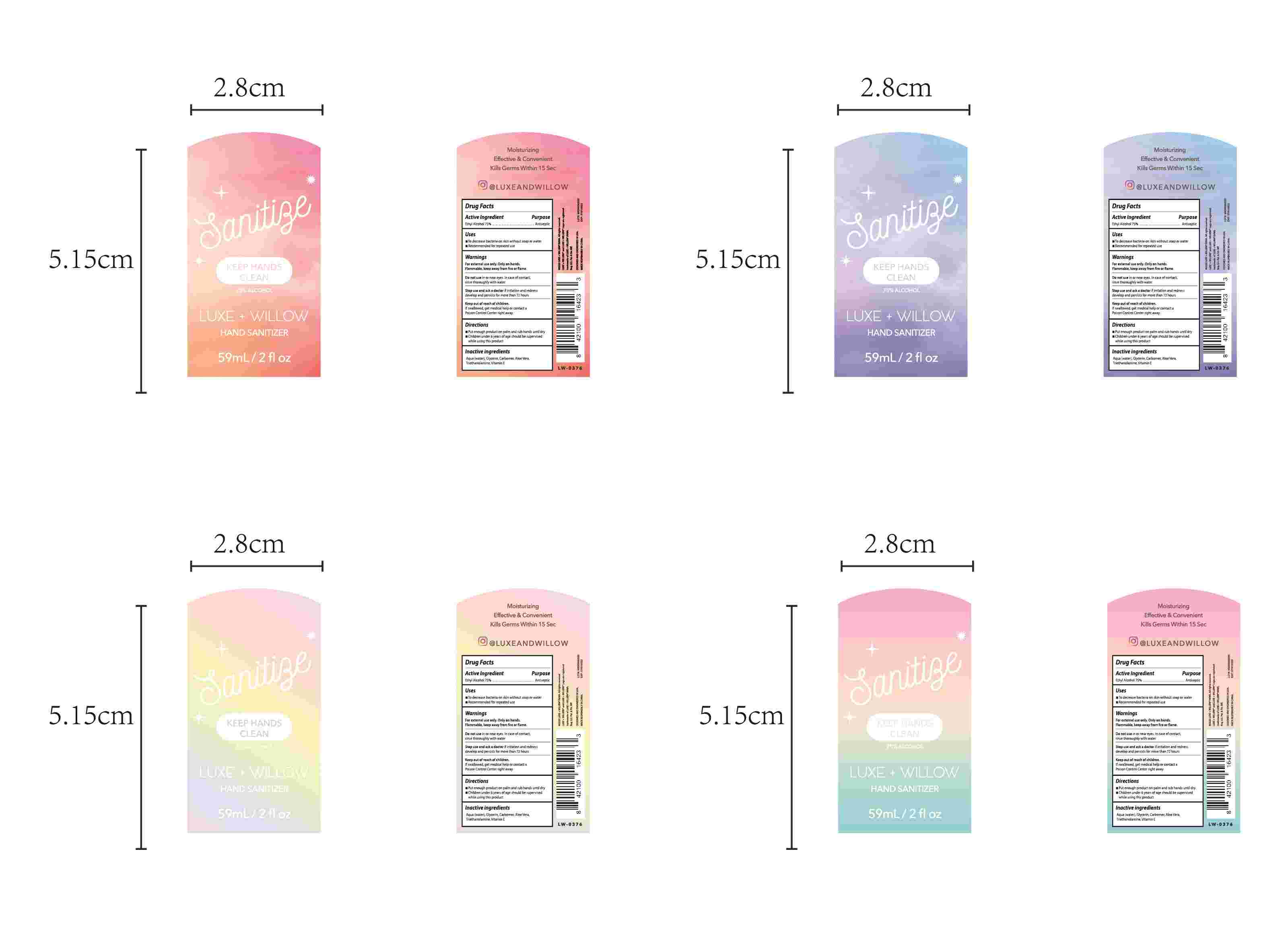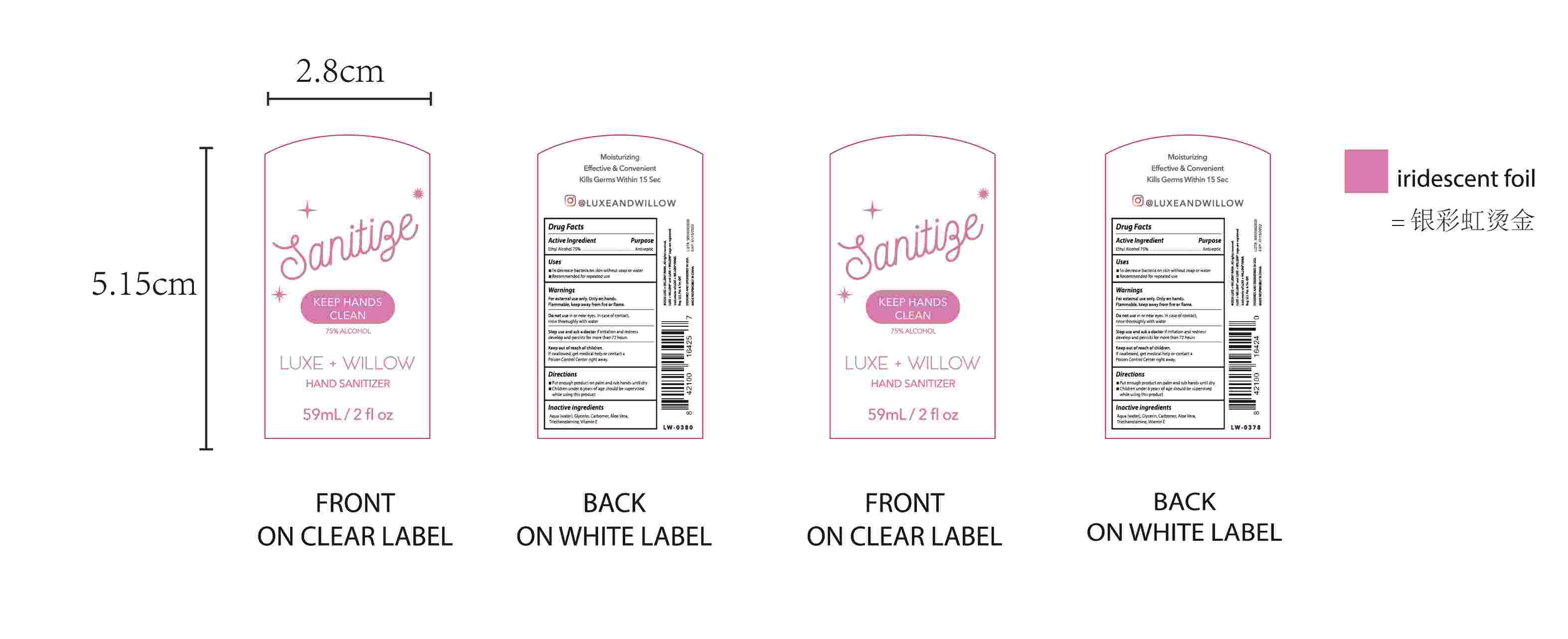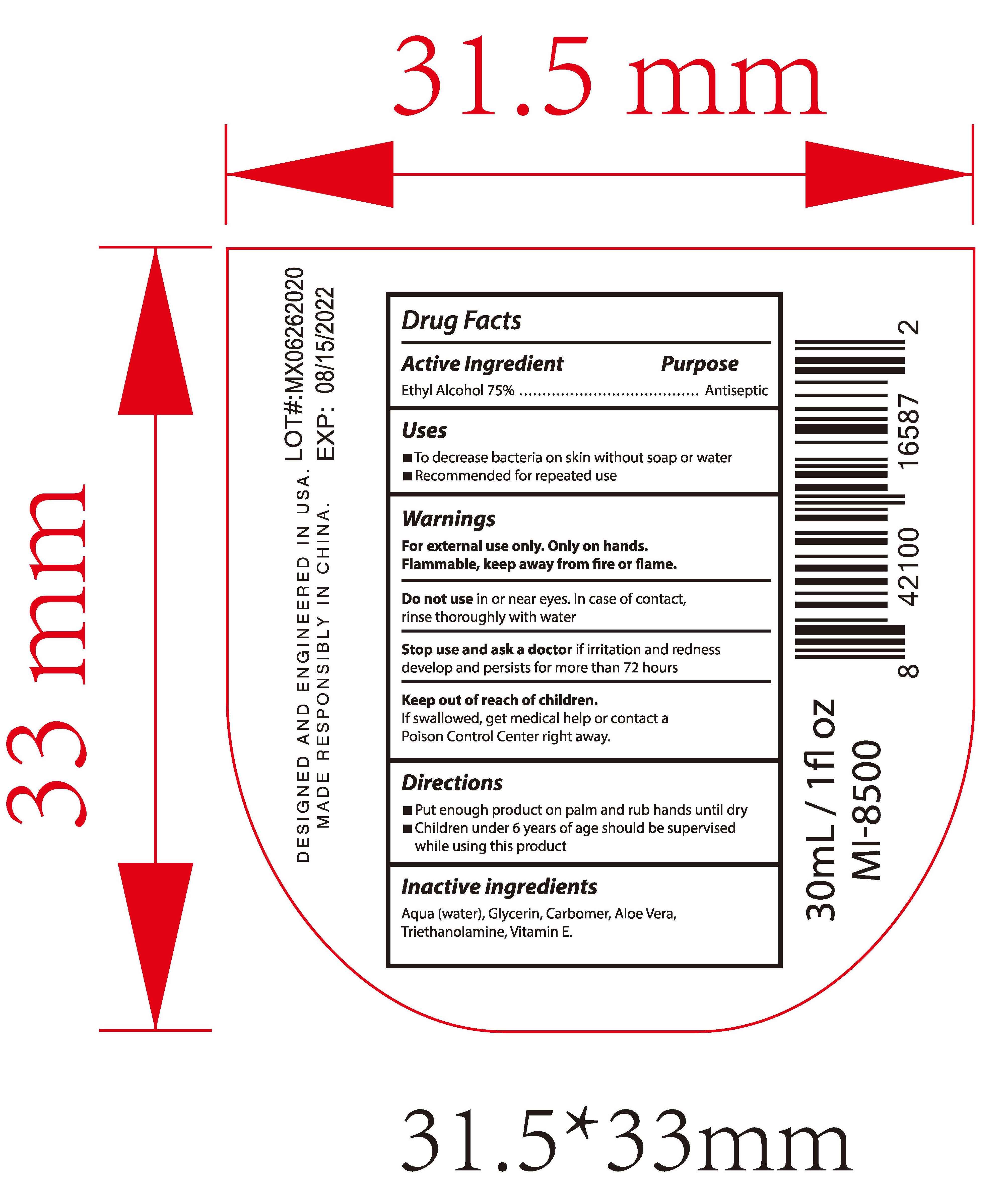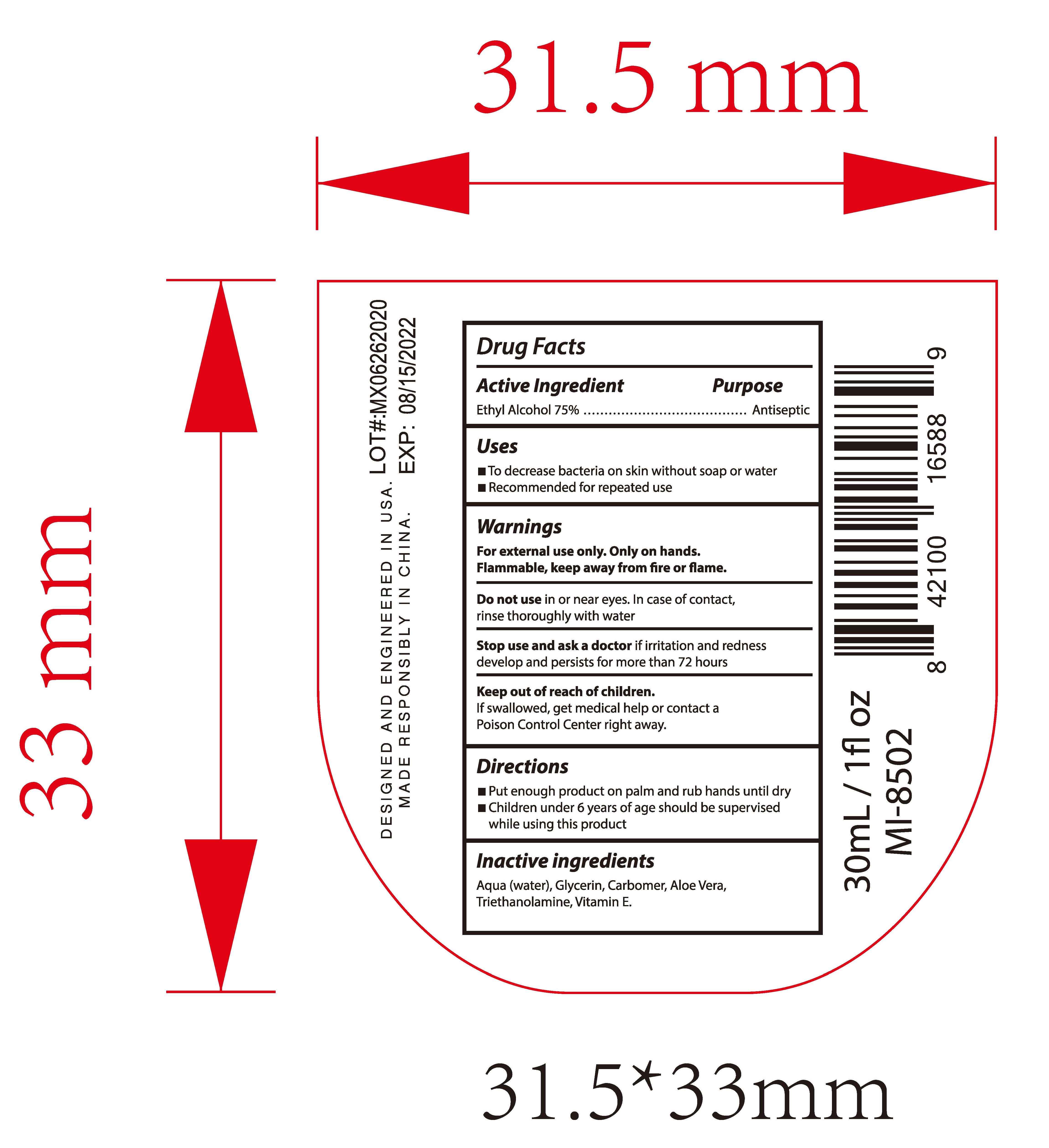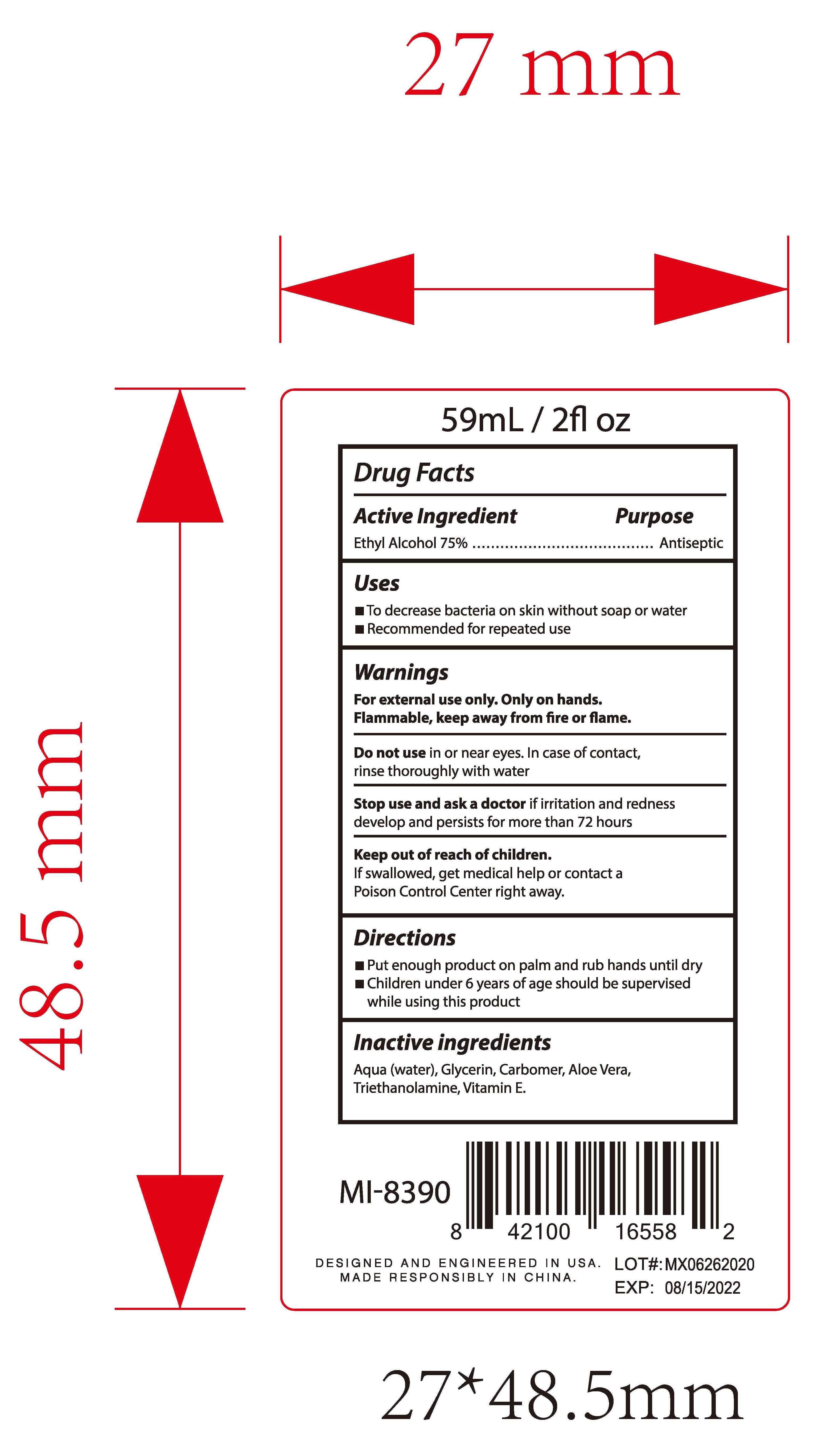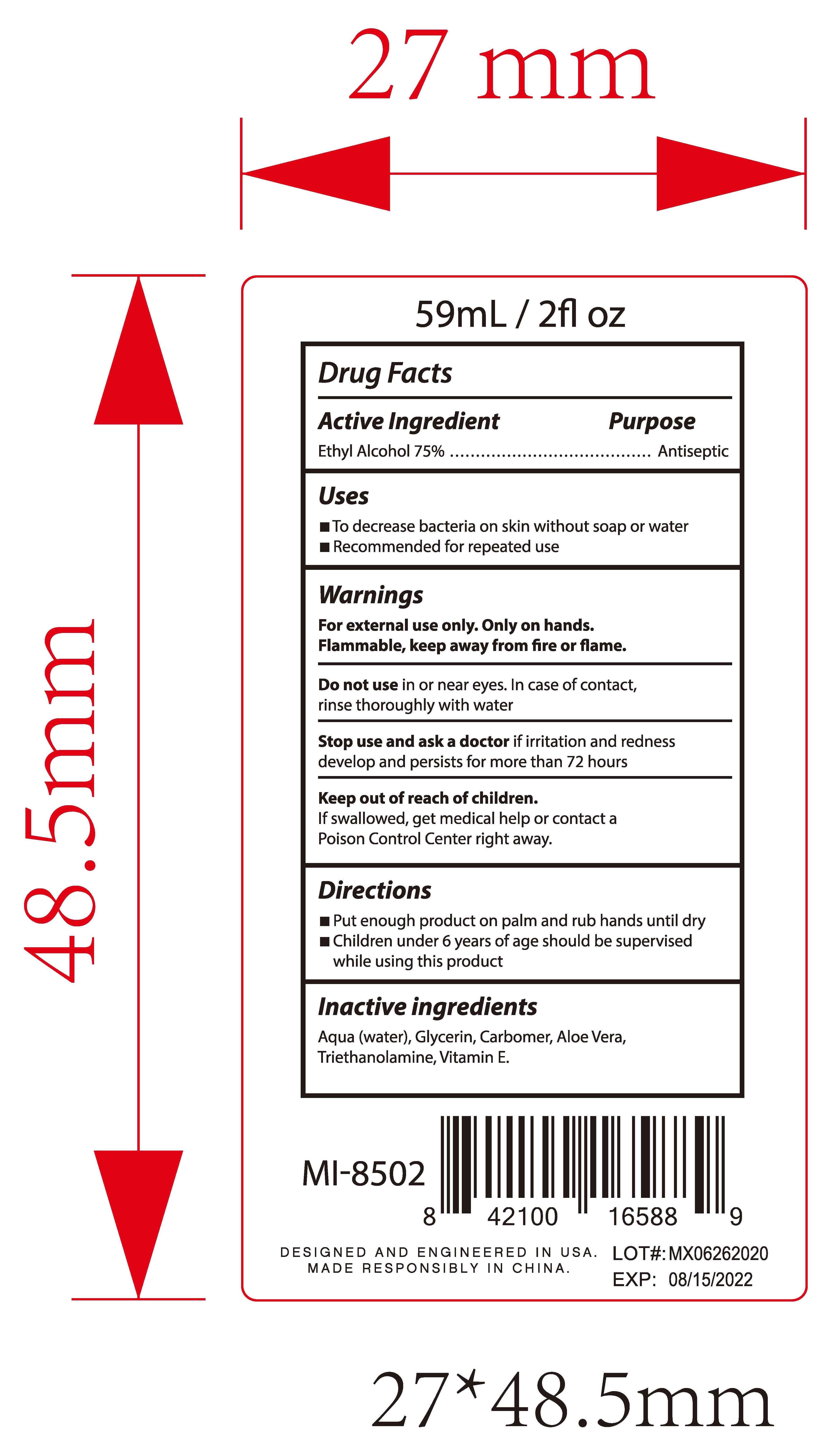 DRUG LABEL: Hand Sanitizer
NDC: 78565-003 | Form: GEL
Manufacturer: Meixin Beauty & Health Care Products Co., Ltd.
Category: otc | Type: HUMAN OTC DRUG LABEL
Date: 20220402

ACTIVE INGREDIENTS: ALCOHOL 75 mL/100 mL
INACTIVE INGREDIENTS: TROLAMINE; ALOE VERA LEAF; .ALPHA.-TOCOPHEROL SUCCINATE, D-; GLYCERIN; CARBOMER HOMOPOLYMER, UNSPECIFIED TYPE; WATER

003 Hand Sanitizer

Active Ingredient(s)

Ethyl Alcohol 75% v/v

Purpose

Antimicrobial

do not use in or near the eyes.

When using this product do not use in or near the eyes.
In case of contact, rinse eyes thoroughly with water.

Stop use and ask a doctor if irritation or rash appears and lasts.

Keep out of reach of children. If swallowed, get medical help or contact a Poison Control Center immediately.

Directions

Put enough product in your palm to cover hands and rubands together briskly until dry.
Children under 6 years of age should be supervised when using.

Other information

Store below 110°F(43°C)

Inactive ingredients

Water, Glycerin, Carbomer, Aloe Vera, Trithanolamine, Vitamine E

INDICATIONS AND USAGE

Hand sanitizer to help reduce bacteria on skin.